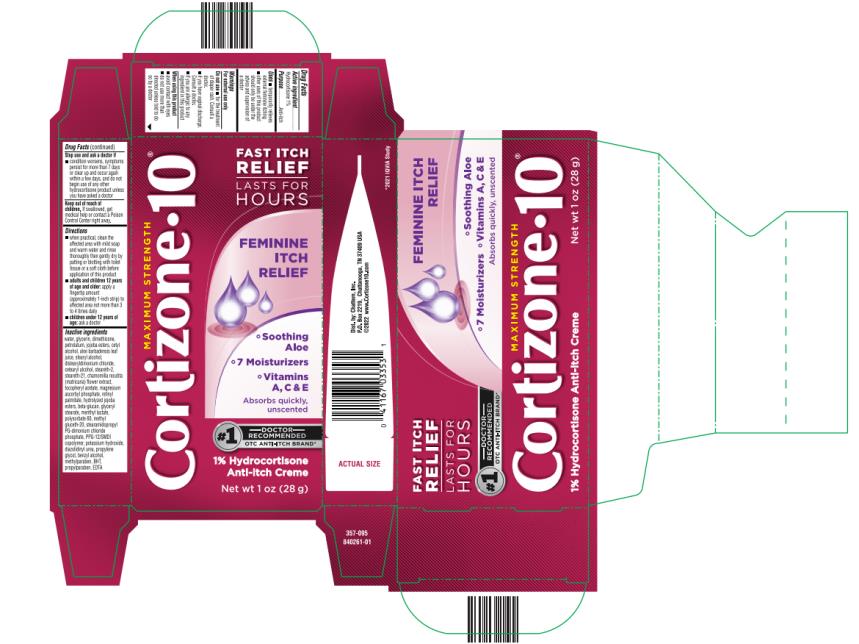 DRUG LABEL: Cortizone 10 Feminine Itch Relief
NDC: 41167-0330 | Form: CREAM
Manufacturer: Chattem, Inc.
Category: otc | Type: HUMAN OTC DRUG LABEL
Date: 20231026

ACTIVE INGREDIENTS: HYDROCORTISONE 1 g/100 g
INACTIVE INGREDIENTS: WATER; GLYCERIN; DIMETHICONE; PETROLATUM; JOJOBA OIL, RANDOMIZED; CETYL ALCOHOL; ALOE VERA LEAF; STEARYL ALCOHOL; DISTEARYLDIMONIUM CHLORIDE; CETOSTEARYL ALCOHOL; STEARETH-2; STEARETH-21; CHAMOMILE; .ALPHA.-TOCOPHEROL ACETATE; MAGNESIUM ASCORBYL PHOSPHATE; VITAMIN A PALMITATE; HYDROLYZED JOJOBA ESTERS (ACID FORM); TRANSFORMING GROWTH FACTOR BETA RECEPTOR TYPE 3; GLYCERYL MONOSTEARATE; MENTHYL LACTATE, (-)-; POLYSORBATE 60; METHYL GLUCETH-20; STEARAMIDOPROPYL PG-DIMONIUM CHLORIDE PHOSPHATE; PPG-12/SMDI COPOLYMER; POTASSIUM HYDROXIDE; DIAZOLIDINYL UREA; PROPYLENE GLYCOL; BENZYL ALCOHOL; METHYLPARABEN; BUTYLATED HYDROXYTOLUENE; PROPYLPARABEN; EDETIC ACID

Cortizone 10 Feminine Itch Relief

Cortizone 10

Feminine Itch Relief

Drug Facts

Active ingredient

Hydrocortisone 1%

Purpose

Anti-itch

Uses

■ temporarily relieves external feminine itching

■ other uses of this product should only be under the advice and supervision of a doctor

Warnings

For external use only

Do not use

■ for the treatment of diaper rash. Consult a doctor. ■ if you have vaginal discharge. Consult a doctor. ■ if you are allergic to any ingredient in this product

When using this product

■ avoid contact with eyes ■ do not use more than directed unless told to do so by a doctor

Stop use and ask a doctor if

■ condition worsens, symptoms persist for more than 7 days or clear up and occur again within a few days, and do not begin use of any other hydrocortisone product unless you have asked a doctor

Keep out of reach of children.

If swallowed, get medical help or contact a Poison Control Center right away.

Directions

■ when practical, clean the affected area with mild soap and warm water and rinse thoroughly then gently dry by patting or blotting with toilet tissue or a soft cloth before application of this product

■ adults and children 12 years of age and older: apply a fingertip amount (approximately 1-inch strip) to affected area not more than 3 to 4 times daily

■ children under 12 years of age: ask a doctor

Inactive ingredients

water, glycerin, dimethicone, petrolatum, jojoba esters, cetyl alcohol, aloe barbadensis leaf juice, stearyl alcohol, distearyldimonium chloride, cetearyl alcohol, steareth-2, steareth-21, chamomilla recutita (matricaria) flower extract, tocopheryl acetate, magnesium ascorbyl phosphate, retinyl palmitate, hydrolyzed jojoba esters, beta-glucan, glyceryl stearate, menthyl lactate, polysorbate 60, methyl gluceth-20, stearamidopropyl PG-dimonium chloride phosphate, PPG-12/SMDI copolymer, potassium hydroxide, diazolidinyl urea, propylene glycol, benzyl alcohol, methylparaben, BHT, propylparaben, EDTA

PRINCIPAL DISPLAY PANEL

Cortizone 10
FAST ITCH RELIEF
LAST FOR HOURS
FEMININE ITCH
RELIEF
1% Hydrocortisone
Anti-Itch Crème
Net wt 1 oz (28 g)